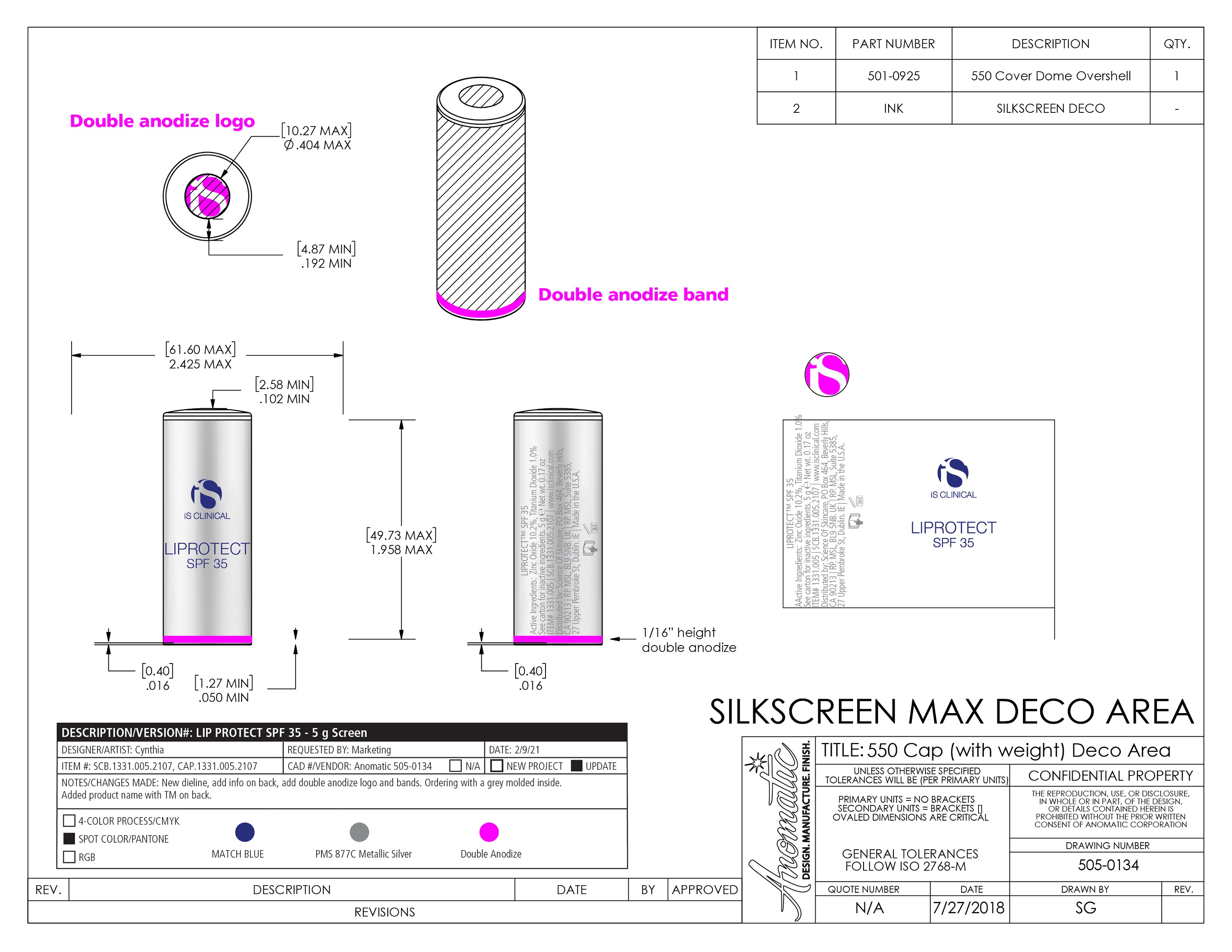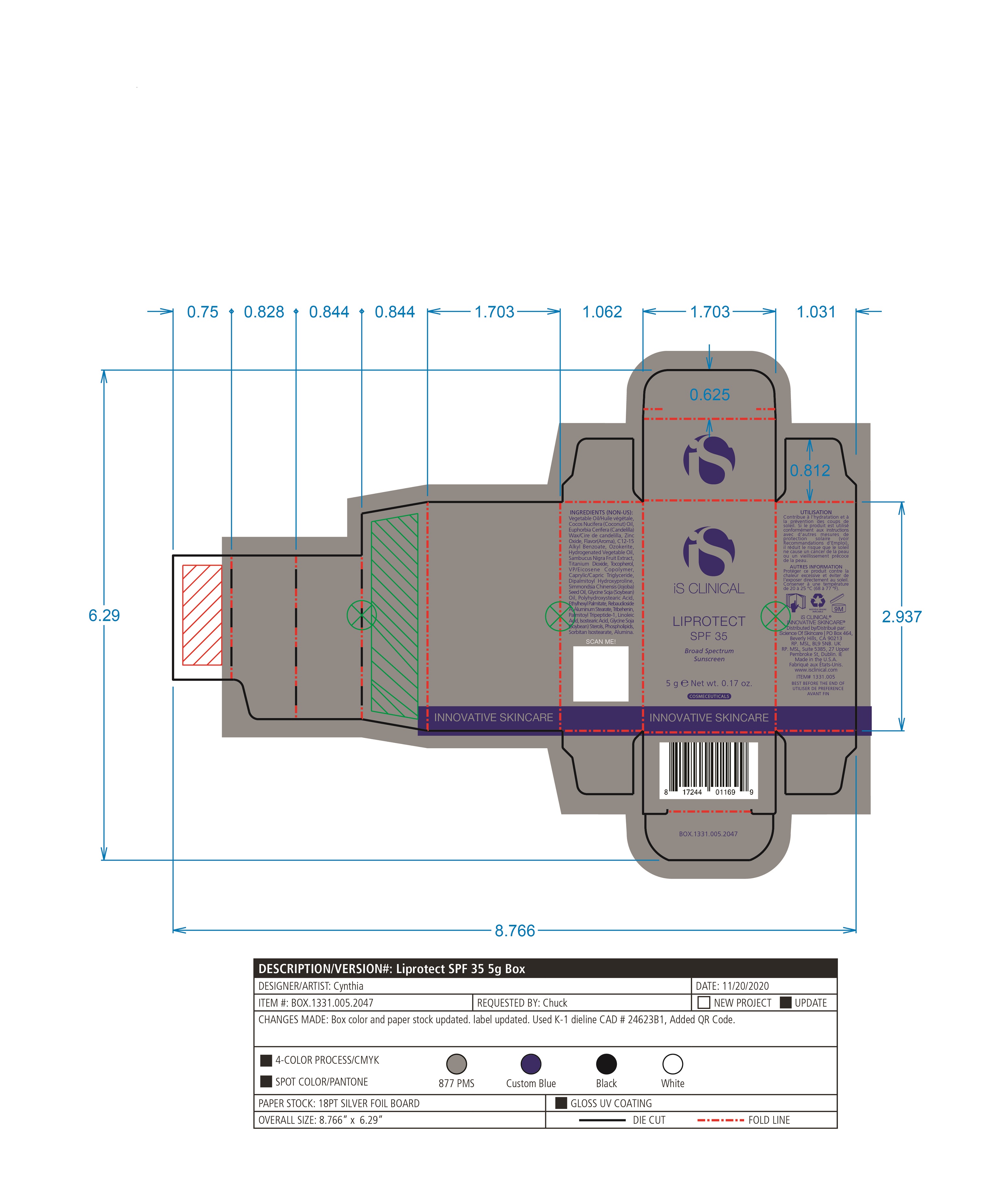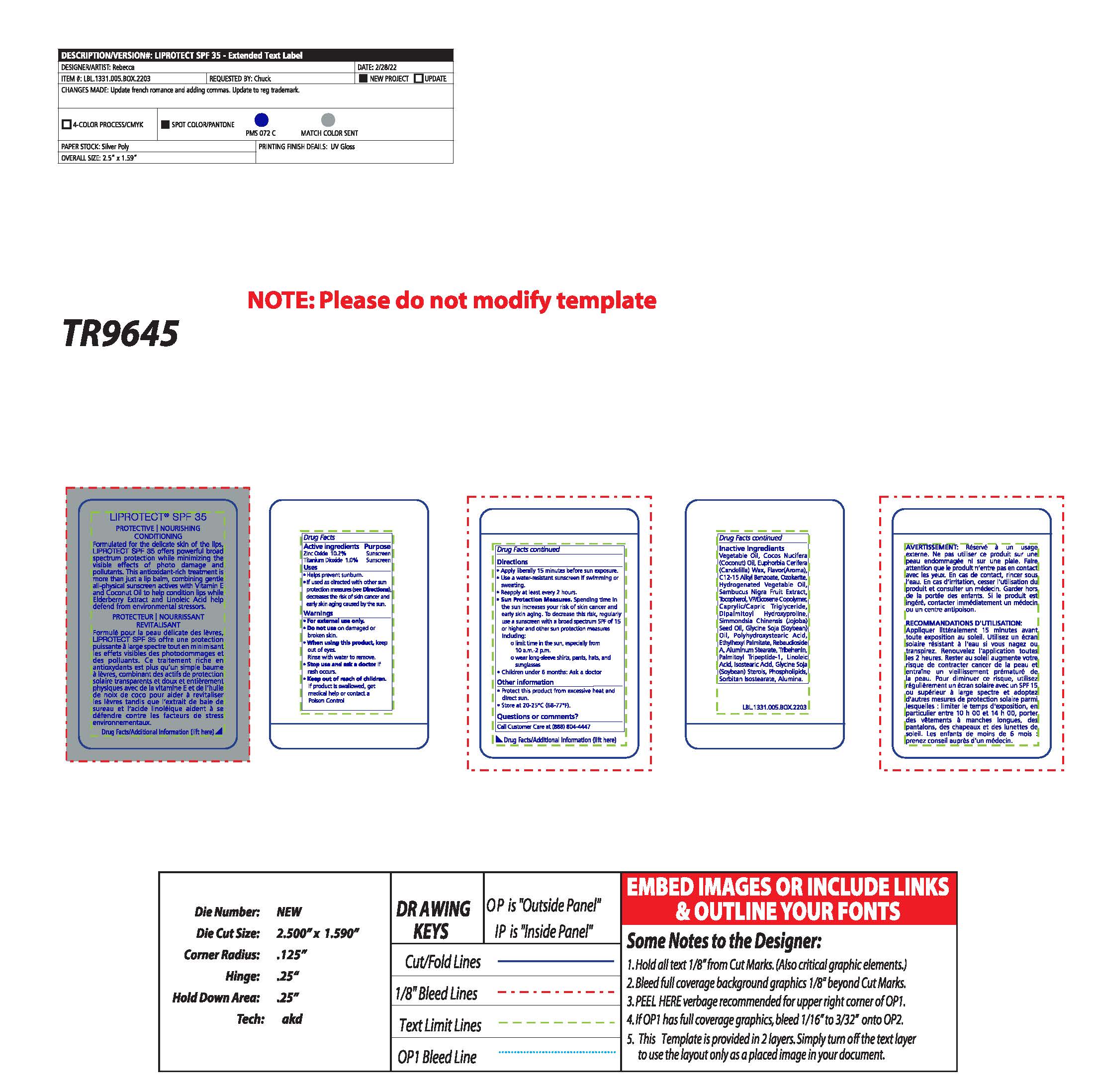 DRUG LABEL: LiProtect SPF 35
NDC: 69219-112 | Form: STICK
Manufacturer: Science of Skincare
Category: otc | Type: HUMAN OTC DRUG LABEL
Date: 20250129

ACTIVE INGREDIENTS: ZINC OXIDE 10.2 g/100 g; TITANIUM DIOXIDE 1 g/100 g
INACTIVE INGREDIENTS: REBAUDIOSIDE A; ISOSTEARIC ACID; SOY STEROL; ALUMINUM OXIDE; MEDIUM-CHAIN TRIGLYCERIDES; DIPALMITOYL HYDROXYPROLINE; LINOLEIC ACID; EUROPEAN ELDERBERRY; COCONUT OIL; CANDELILLA WAX; ALKYL (C12-15) BENZOATE; OMEGA-3 FATTY ACIDS; SORBITAN ISOSTEARATE; TRIBEHENIN; SOYBEAN OIL; CERESIN; CHERRY; EICOSYL POVIDONE; ETHYLHEXYL PALMITATE; ALUMINUM STEARATE; PALMITOYL TRIPEPTIDE-1; TOCOPHEROL; JOJOBA OIL; POLYHYDROXYSTEARIC ACID (2300 MW); CORN OIL

LiProtect SPF 35 (69219-112)

ACTIVE INGREDIENT

Zinc Oxide 10.2%

Titanium Dioxide 1.0%

PURPOSE

Sunscreen

INDICATIONS AND USAGE

Helps prevent sunburn

If used as directed with other sun protection measures (see Directions), decreases the risk of skin cancer and early skin aging caused by the sun.

WARNINGS

For external use only.

When using this product keep out of eyes. Rinse with water to remove.

Do not use on damaged or broken skin

Keep out of reach of children. If product is swallowed, get medical help or contact a Poison Control Center right away.

Stop use and ask a doctor if rash occurs.

DOSAGE AND ADMINISTRATION

Apply liberally 15 minutes before sun exposure

Use a water resistance sunscreen if swimming or sweating.

Reapply at least every 2 hours

Sun Protection Measures. Spending time in the sun increases your risk of skin cancer and early skin aging. To decrease this risk, regularly use a sunscreen with a board spectrum SPF of 15 or higher and other sun protection measures including: limit time in sun, especially from 10am to 2pm. wear long-sleeve shirts, pants, hats, and sunglasses. Children under the age of 6 months. Ask a doctor.

OTHER SAFETY INFORMATION

Protect this product from excessive heat and direct sun.

Store at 20-25C (68 - 77F)

QUESTIONS

Call Customer Care at (888) 804 - 4447

INACTIVE INGREDIENT

Vegetable Oil, Cocos Nucifera (Coconut) Oil, Euphorbia Cerifera (Candelilla) Wax, Flavor(Aroma), C12-15 Alkyl Benzoate, Ozokerite, Hydrogenated Vegetable Oil, Sambucus Nigra Fruit Extract, Tocopherol, VP/Eicosene Copolymer, Caprylic/Capric Triglyceride, Dipalmitoyl Hydroxyproline, Simmondsia Chinensis (Jojoba) Seed Oil, Glycine Soja (Soybean) Oil, Polyhydroxystearic Acid, Ethylhexyl Palmitate, Rebaudioside A, Aluminum Stearate, Tribehenin, Palmitoyl Tripeptide-1, Linoleic Acid, Isostearic Acid, Glycine Soja (Soybean) Sterols, Phospholipids, Sorbitan Isostearate, Alumina.